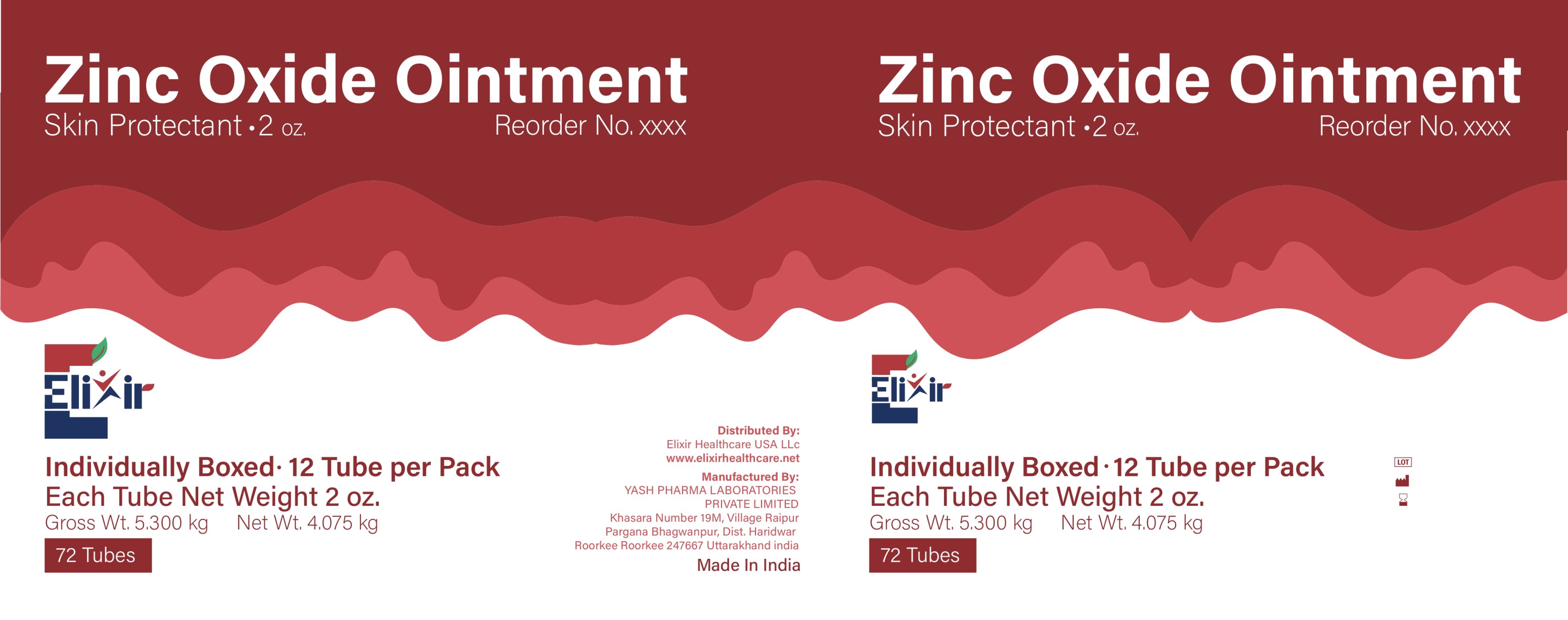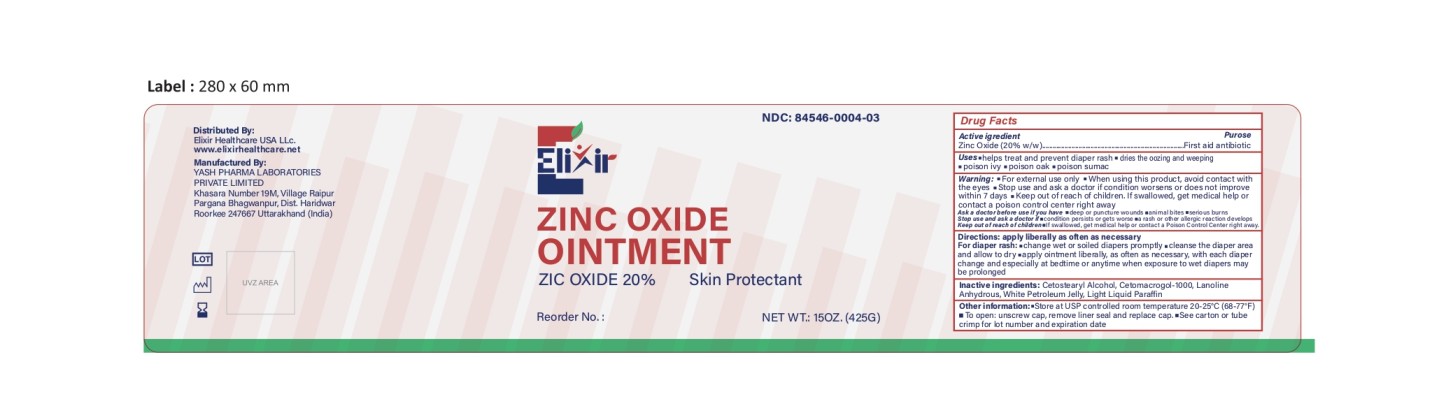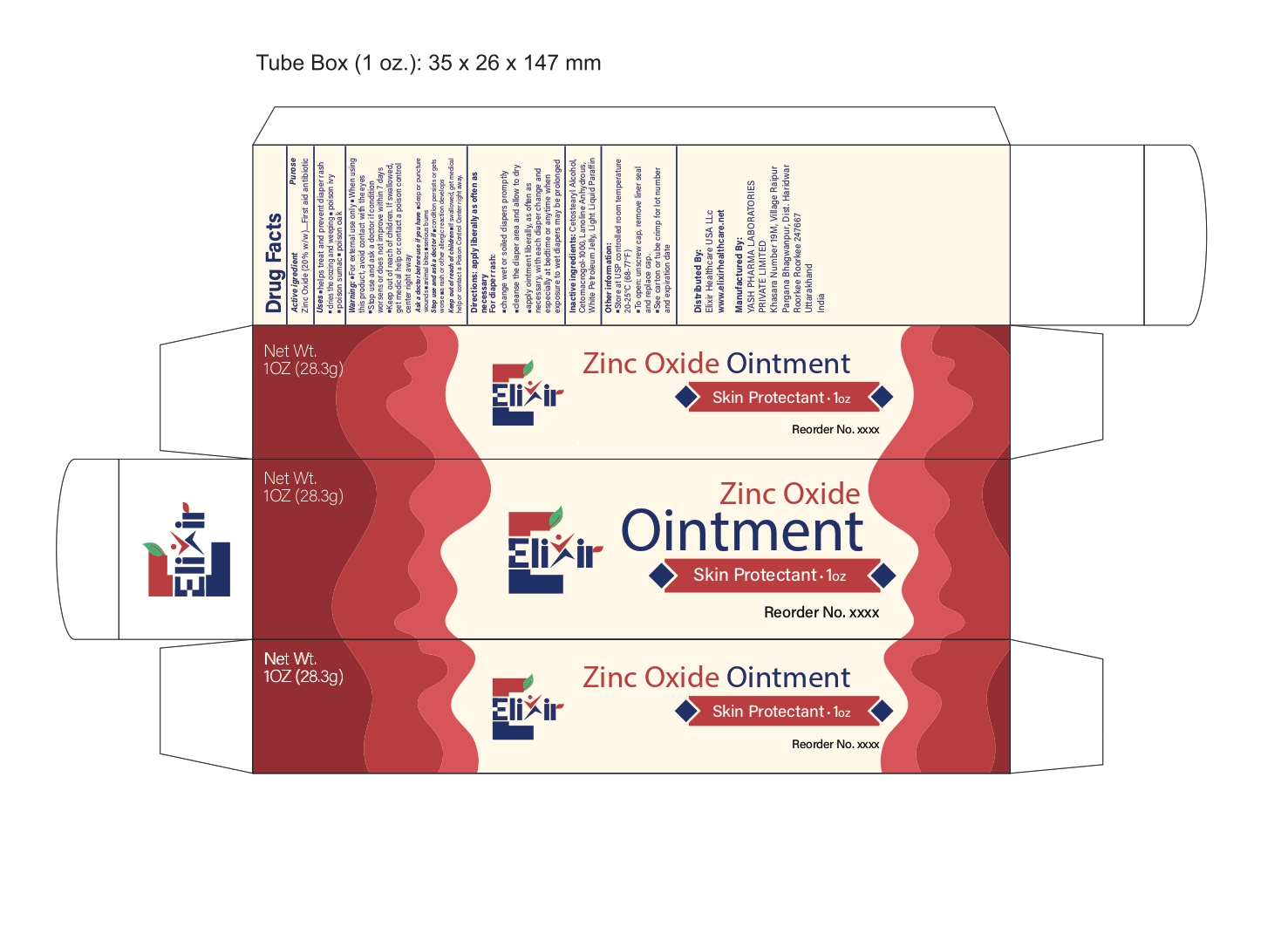 DRUG LABEL: ElixirZincoCare
NDC: 84546-0004 | Form: OINTMENT
Manufacturer: ELIXIR HEALTHCARE USA, LLC.
Category: otc | Type: HUMAN OTC DRUG LABEL
Date: 20251122

ACTIVE INGREDIENTS: ZINC OXIDE 20 g/100 g
INACTIVE INGREDIENTS: CETOSTEARYL ALCOHOL; CETETH-20; WHITE PETROLATUM; PARAFFIN

Drug Facts

Active Ingredient (in each gram)

Zinc Oxide 20% w/w

Purpose

First Aid Antibiotic

Uses

helps treat and prevent diaper rash. Protects chafed skin due to diaper rash and helps seal out wetness. dries the oozing and weeping of poison ivy, poison oak and poison sumac

Warnings

For external use only

Do not use

• For external use only
• When using this product, avoid contact with the eyes
• Stop use and ask a doctor if condition worsens or does not improve within 7 days
Keep out of reach of children. If swallowed, get medical help or contact a poison control center right away

Ask a doctor before use in case of

• deep or puncture wounds
• animal bites
• serious burns

Stop use and ask a doctor if

• condition persists or gets worse
• a rash or other allergic reaction develops

Keep out of reach of children

If swallowed, get medical help or contact a Poison Control Center right away.

Directions

apply liberally as often as necessary
For diaper rash:
• change wet or soiled diapers promptly
• cleanse the diaper area and allow to dry
• apply ointment liberally, as often as necessary, with each diaper change and especially at bedtime or anytime when exposure to wet diapers may be prolonged

Inactive ingredients

Cetostearyl Alcohol, Cetomacrogol-1000, Lanoline Anhydrous, White Petroleum Jelly, Light Liquid Paraffin

Other information

• Store at USP controlled room temperature 20-25°C (68-77°F)
• To open: unscrew cap, remove liner seal and replace cap.
• see carton or tube crimp for lot number and expiration date

PRINCIPAL DISPLAY PANEL

Zinc Oxide Ointment

Skin Protectant • 2 oz

Reorder No. xxxx

Individually Boxed • 12 Tubes per Pack

Each Tube Net Weight 2 oz

Gross Wt. 5.300 kg Net Wt. 4.075 kg

72 Tubes

Elixir

PRINCIPAL DISPLAY PANEL

Zinc Oxide Ointment

Skin Protectant • 1 oz

Net Wt. 1 OZ (28.3 g)

Reorder No. xxxx

Elixir

PRINCIPAL DISPLAY PANEL

ZINC OXIDE OINTMENT

ZINC OXIDE 20%

Skin Protectant

15 OZ. Jars • 12 Jars per Case

Reorder No.: ______